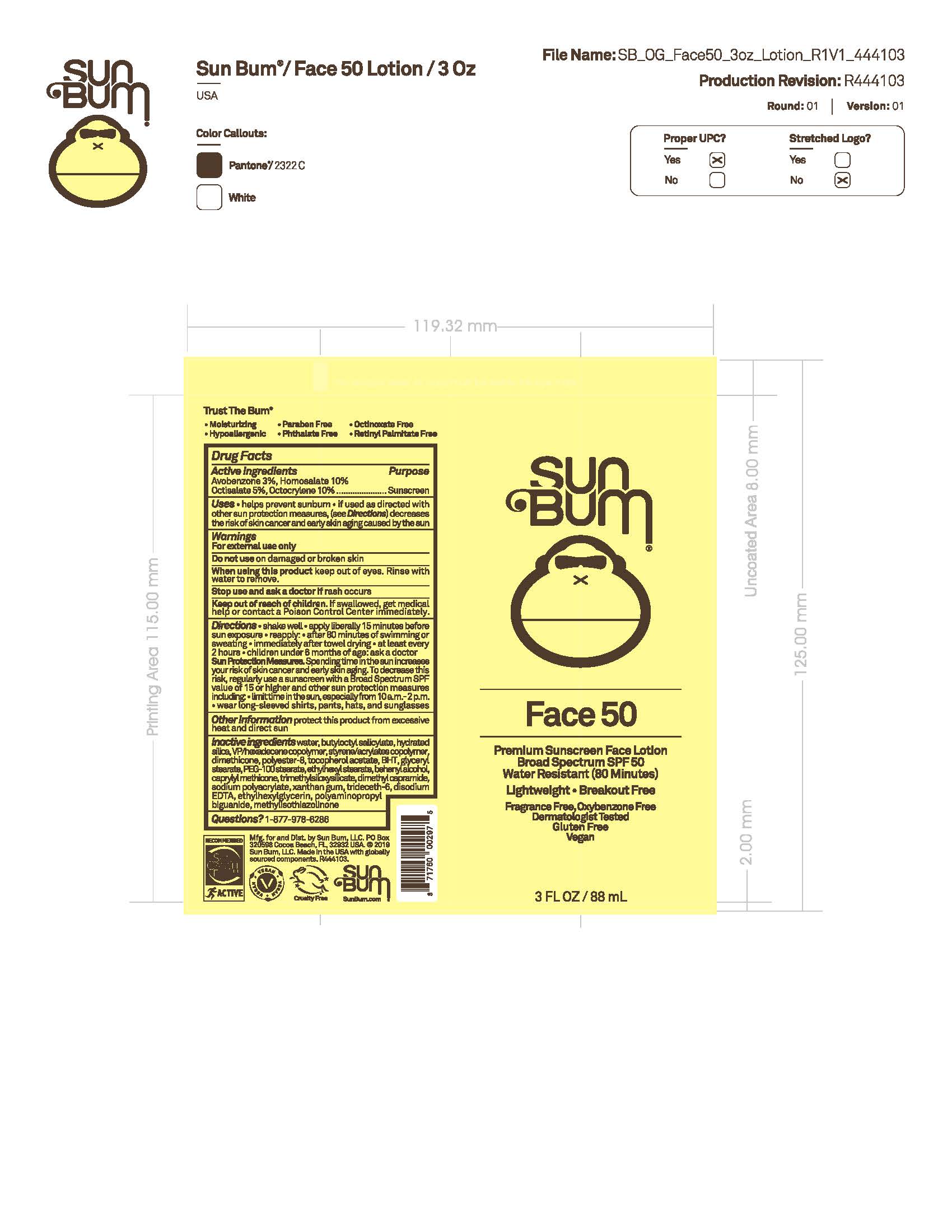 DRUG LABEL: Sun Bum Face 50 Premium Sunscreen SPF 50
NDC: 44717-080 | Form: LOTION
Manufacturer: Wasatch Product Development, LLC
Category: otc | Type: HUMAN OTC DRUG LABEL
Date: 20251010

ACTIVE INGREDIENTS: AVOBENZONE 3 g/100 mL; HOMOSALATE 10 g/100 mL; OCTISALATE 5 g/100 mL; OCTOCRYLENE 10 g/100 mL
INACTIVE INGREDIENTS: VINYLPYRROLIDONE/HEXADECENE COPOLYMER; DIMETHICONE; .ALPHA.-TOCOPHEROL ACETATE; BUTYLATED HYDROXYTOLUENE; GLYCERYL MONOSTEARATE; PEG-100 STEARATE; ETHYLHEXYL STEARATE; DOCOSANOL; CAPRYLYL TRISILOXANE; DIMETHYL CAPRAMIDE; XANTHAN GUM; TRIDECETH-6; EDETATE DISODIUM ANHYDROUS; ETHYLHEXYLGLYCERIN; METHYLISOTHIAZOLINONE; SODIUM POLYACRYLATE (8000 MW); POLYAMINOPROPYL BIGUANIDE; TRIMETHYLSILOXYSILICATE (M/Q 0.6-0.8); POLYESTER-8 (1400 MW, CYANODIPHENYLPROPENOYL CAPPED); WATER; BUTYLOCTYL SALICYLATE; HYDRATED SILICA

Sun Bum Face 50 Premium Sunscreen Lotion SPF 50

Active ingredients Purpose

Avobenzone 3 %, Homosalate 10%

Octisalate 5.%, Octocrylene 10% Sunscreen

Uses

- helps prevent sunburn.
- If used as directed with other sun protection measures (see Directions), decreases the risk of skin cancer and early skin aging caused by the sun.

Keep out of reach of children. If swallowed, get medical help or contact a Poison Control Center immediately.

Stop use and ask a doctor if rash occurs.

Warnings

For external use only

Do not use on damaged or broken skin.

When using this product: Keep out of eyes. Rinse with water to remove.

Directions

- shake well
- apply liberally 15 minutes before sun exposure.
- reapply: after 80 minutes of swimming or sweating
- immediately after towel drying.
- at least every 2 hours.
- children under 6 months of age: ask a doctor.
- Sun Protection Measures. Spending time in the sun increases your risk of skin cancer and early skin aging, to decrease this risk, regularly use a sunscreen with a Broad Spectrum SPF of 15 or higher and other sun protection measures, including:
- limit time in the sun, especially from 10 a.m. - 2 p.m.
- wear long-sleeve shirts, pants, hats, and sunglasses.

Other information

protect this product from excessive heat and direct sun.

INACTIVE INGREDIENT

Inactive Ingredients water, butyloctyl salicylate, hydrated silica, VP/hexadecene copolymer, styrene/acrylates copolymer, dimethicone, polyester-8, tocopherol acetate, BHT, glyceryl stearate, PEG-100 stearate, ethylhexyl stearate, behenyl alcohol, caprylyl methicone, trimethylsiloxysilicate, dimethyl capramide, sodium polyacrylate, xanthan gum, trideceth-6, disodium EDTA, ethylhexylglycerin, polyaminopropyl biguanide, methylisothiazolinone

PACKAGE LABEL

Sun Bum

Face 50

Premium Sunscreen Face Lotion

Broad Spectrum SPF 50

Water Resistant (80 Minutes)

Lightweight

Breakout Free

Fragrance Free, Oxbenzone Free

Dermatologist Tested

Gluten Free

Vegan

3 FL OZ / 88 mL